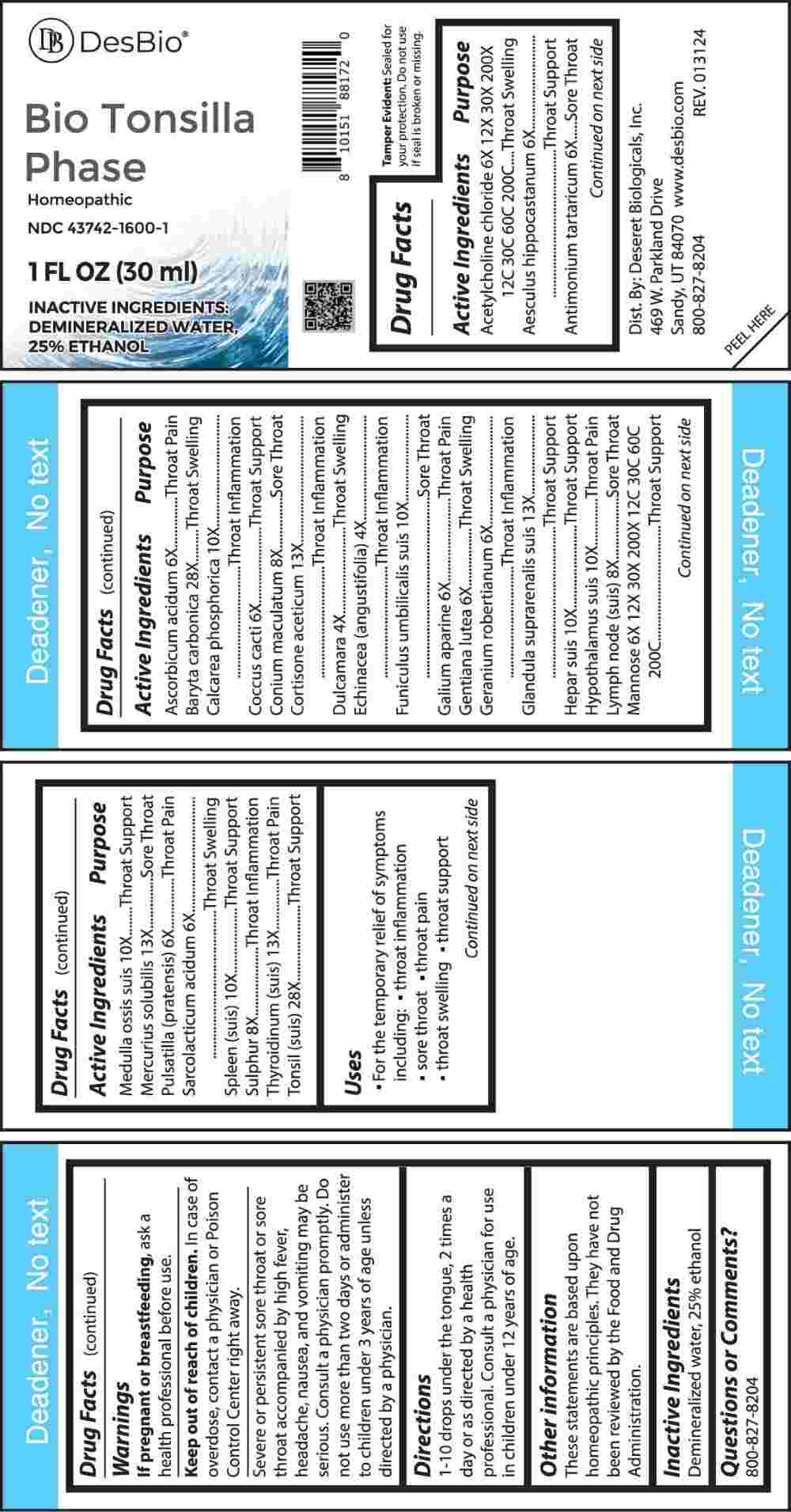 DRUG LABEL: Bio Tonsilla Phase
NDC: 43742-1600 | Form: LIQUID
Manufacturer: Deseret Biologicals, Inc.
Category: homeopathic | Type: HUMAN OTC DRUG LABEL
Date: 20240507

ACTIVE INGREDIENTS: SOLANUM DULCAMARA TOP 4 [hp_X]/1 mL; ECHINACEA ANGUSTIFOLIA WHOLE 4 [hp_X]/1 mL; HORSE CHESTNUT 6 [hp_X]/1 mL; ANTIMONY POTASSIUM TARTRATE 6 [hp_X]/1 mL; ASCORBIC ACID 6 [hp_X]/1 mL; PROTORTONIA CACTI 6 [hp_X]/1 mL; GALIUM APARINE WHOLE 6 [hp_X]/1 mL; GENTIANA LUTEA ROOT 6 [hp_X]/1 mL; GERANIUM ROBERTIANUM WHOLE 6 [hp_X]/1 mL; PULSATILLA PRATENSIS WHOLE 6 [hp_X]/1 mL; LACTIC ACID, L- 6 [hp_X]/1 mL; ACETYLCHOLINE CHLORIDE 6 [hp_X]/1 mL; MANNOSE, D- 6 [hp_X]/1 mL; CONIUM MACULATUM FLOWERING TOP 8 [hp_X]/1 mL; SUS SCROFA LYMPH 8 [hp_X]/1 mL; SULFUR 8 [hp_X]/1 mL; TRIBASIC CALCIUM PHOSPHATE 10 [hp_X]/1 mL; SUS SCROFA UMBILICAL CORD 10 [hp_X]/1 mL; PORK LIVER 10 [hp_X]/1 mL; SUS SCROFA HYPOTHALAMUS 10 [hp_X]/1 mL; SUS SCROFA BONE MARROW 10 [hp_X]/1 mL; SUS SCROFA SPLEEN 10 [hp_X]/1 mL; CORTISONE ACETATE 13 [hp_X]/1 mL; SUS SCROFA ADRENAL GLAND 13 [hp_X]/1 mL; MERCURIUS SOLUBILIS 13 [hp_X]/1 mL; SUS SCROFA THYROID 13 [hp_X]/1 mL; BARIUM CARBONATE 28 [hp_X]/1 mL; SUS SCROFA TONSIL 28 [hp_X]/1 mL
INACTIVE INGREDIENTS: WATER; ALCOHOL

DRUG FACTS:

ACTIVE INGREDIENTS:

Acetylcholine Chloride 6X, 12X, 30X, 200X, 12C, 30C, 60C, 200C, Aesculus Hippocastanum 6X, Antimonium Tartaricum 6X, Ascorbicum Acidum 6X, Baryta Carbonica 28X, Calcarea Phosphorica 10X, Coccus Cacti 6X, Conium Maculatum 8X, Cortisone Aceticum 8X, Dulcamara 4X, Echinacea (Angustifolia) 4X, Funiculus Umbilicalis Suis 10X, Galium Aparine 6X, Gentiana Lutea 6X, Geranium Robertianum 6X, Glandula Suprarenalis Suis 13X, Hepar Suis 10X, Hypothalamus Suis 10X, Lymph Node (Suis) 8X, Mannose 6X, 12X, 30X, 200X, 12C, 30C, 60C, 200C, Medulla Ossis Suis 10X, Mercurius Solubilis 13X, Pulsatilla (Pratensis) 6X, Sarcolacticum Acidum 6X, Spleen (Suis) 10X, Sulphur 8X, Thyroidinum (Suis) 13X, Tonsil Suis 28X.

PURPOSE:

Acetylcholine Chloride – Throat Swelling, Aesculus Hippocastanum – Throat Support, Antimonium Tartaricum – Sore Throat, Ascorbicum Acidum – Throat Pain, Baryta Carbonica – Throat Swelling, Calcarea Phosphorica – Throat Inflammation, Coccus Cacti – Throat Support, Conium Maculatum – Sore Throat, Cortisone Aceticum – Throat Inflammation, Dulcamara – Throat Swelling, Echinacea (Angustifolia) – Throat Inflammation, Funiculus Umbilicalis – Sore Throat, Galium Aparine – Throat Pain, Gentiana Lutea – Throat Swelling, Geranium Robertianum – Throat Swelling, Glandula Suprarenalis Suis – Throat Support, Hepar Suis – Throat Support, Hypothalamus Suis – Throat Support, Lymph Node (Suis) – Sore Throat, Mannose – Throat Support, Medulla Ossis Suis – Throat Support, Mercurius Solubilis – Sore Throat, Pulsatilla (Pratensis) – Throat Pain, Sarcolacticum Acidum – Throat Swelling, Spleen (Suis) – Throat Support, Sulphur – Throat Inflammation, Thyroidinum (Suis) – Throat Pain, Tonsil Suis – Throat Support

USES:

• For the temporary relief of symptoms including:

• throat inflammation • sore throat • throat pain

• throat swelling • throat support

These statements are based upon homeopathic principles. They have not been reviewed by the Food and Drug Administration.

WARNINGS:

If pregnant or breast-feeding, ask a health professional before use.

Keep out of reach of children. In case of overdose, contact a physician or Poison Control Center right away.

Tamper Evident: Sealed for your protection.

Do not use if seal is broken or missing.

Severe or persistent sore throat or sore throat accompanied by high fever, headache, nausea, and vomiting may be serious. Consult a physician promptly. Do not use more than two days or administer to children under 3 years of age unless directed by a physician.

KEEP OUT OF REACH OF CHILDREN:

In case of overdose, contact a physician or Poison Control Center right away.

DIRECTIONS:

1-10 drops under the tongue, 2 times a day or as directed by a health professional. Consult a physician for use in children under 12 years of age.

INACTIVE INGREDIENTS:

Demineralized water, 25% ethanol

QUESTIONS:

Dist. By: Deseret Biologicals, Inc.

469 W. Parkland Drive

Sandy, UT 84070

www.desbio.com

800-827-8204

PACKAGE LABEL DISPLAY:

Des Bio

Bio Tonsilla Phase

Homeopathic
NDC 43742-1600-1

1 FL OZ (30 ml)